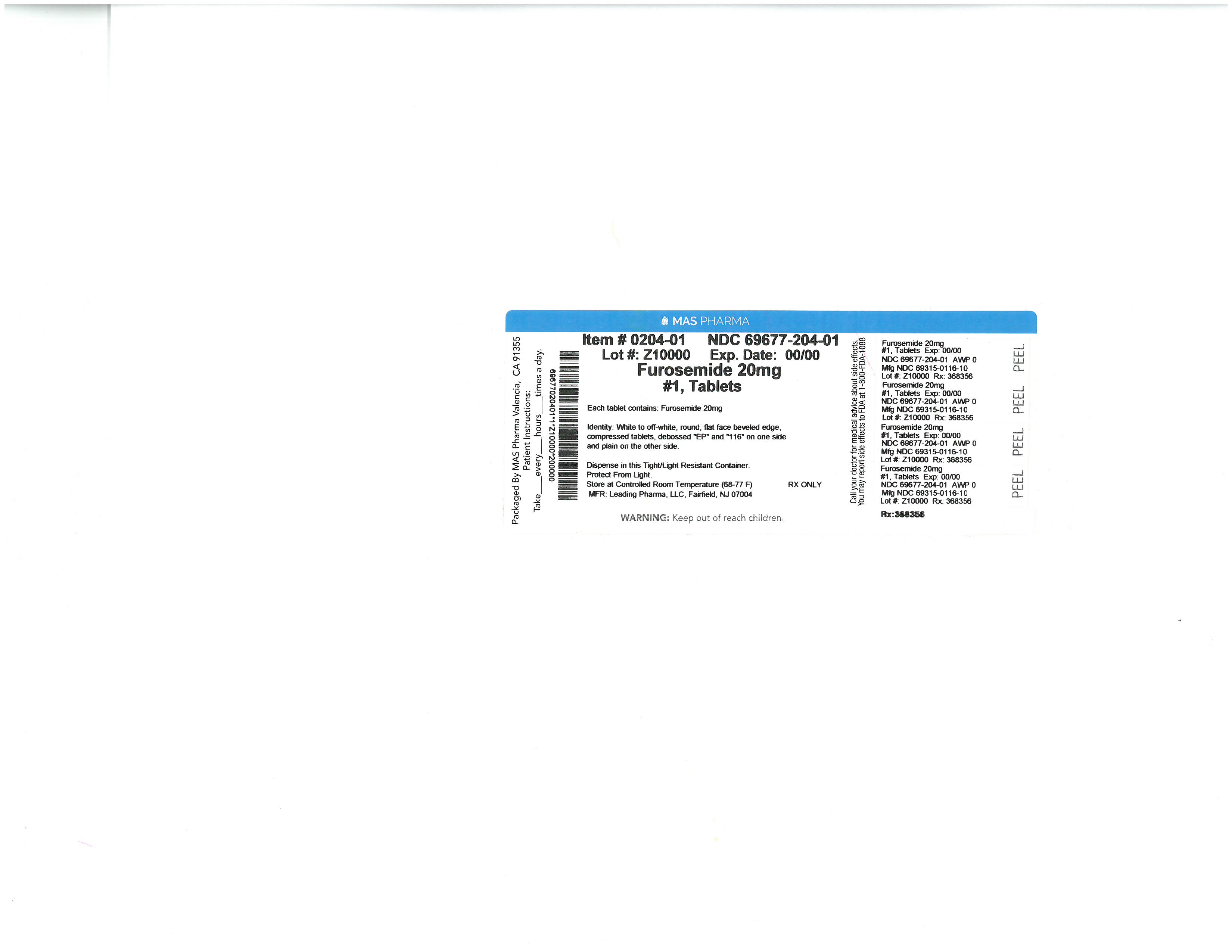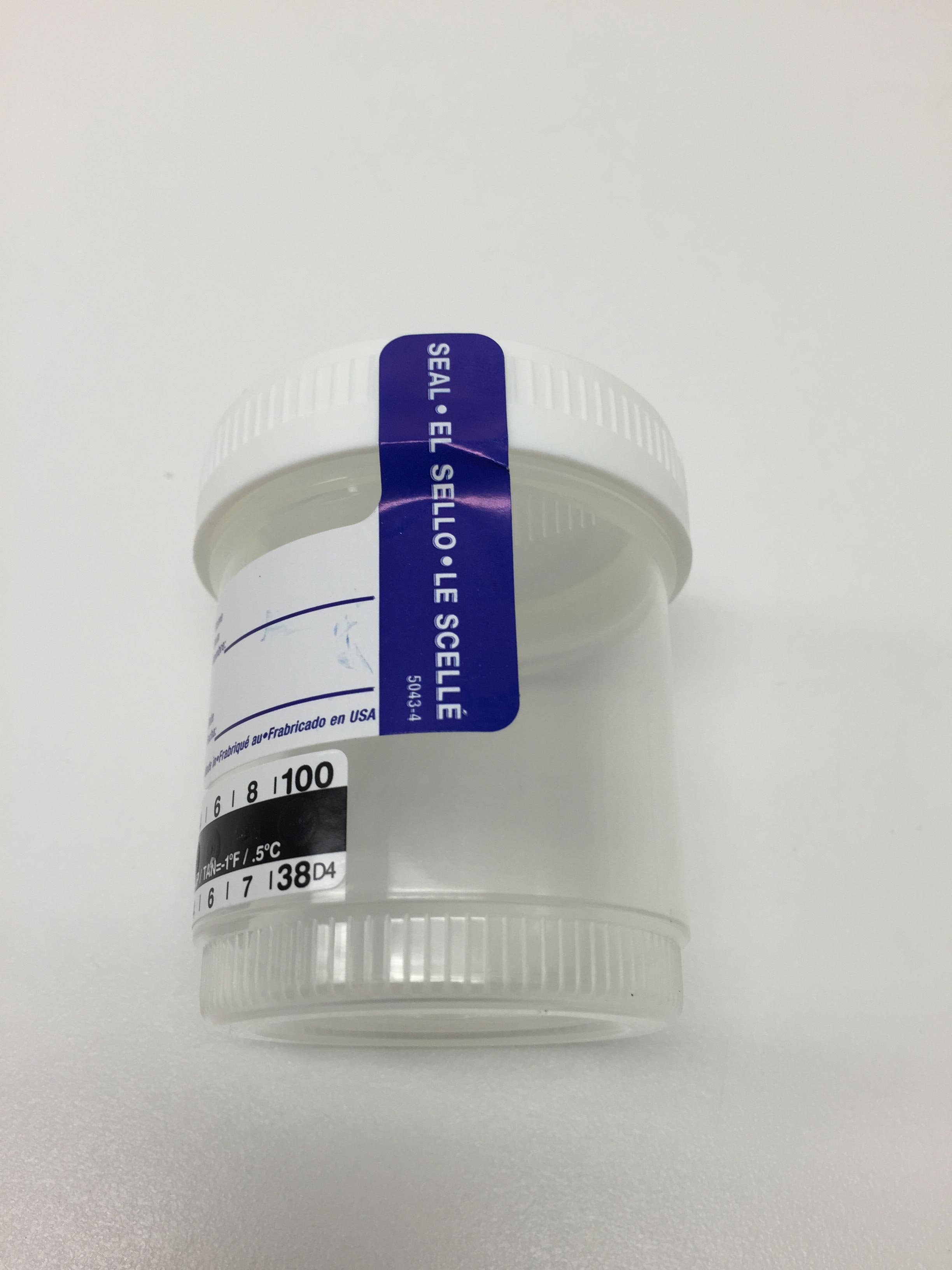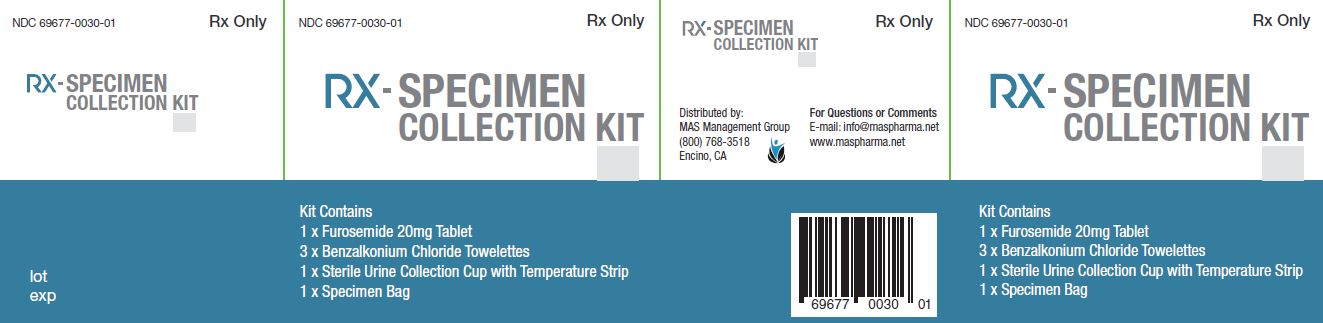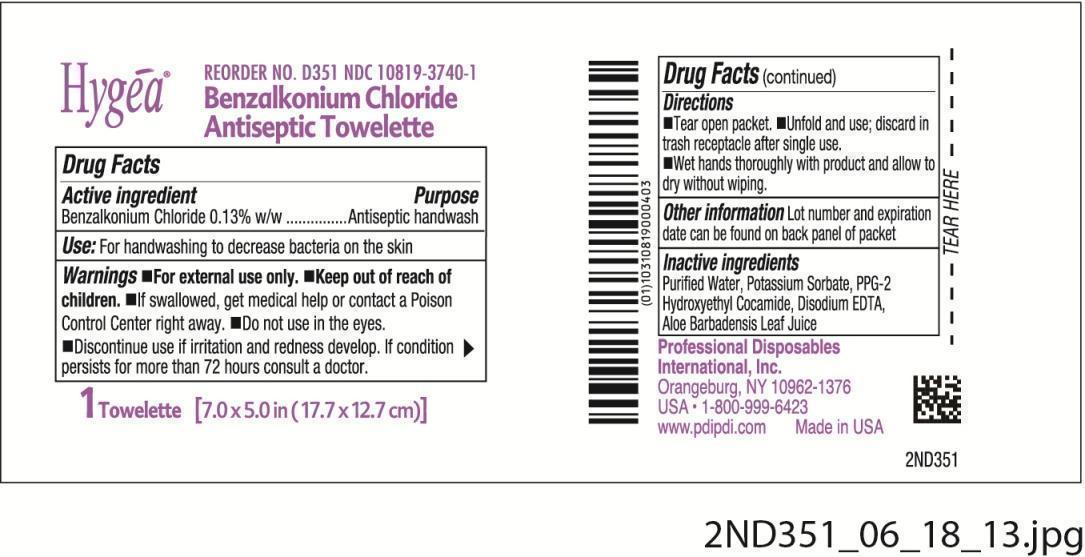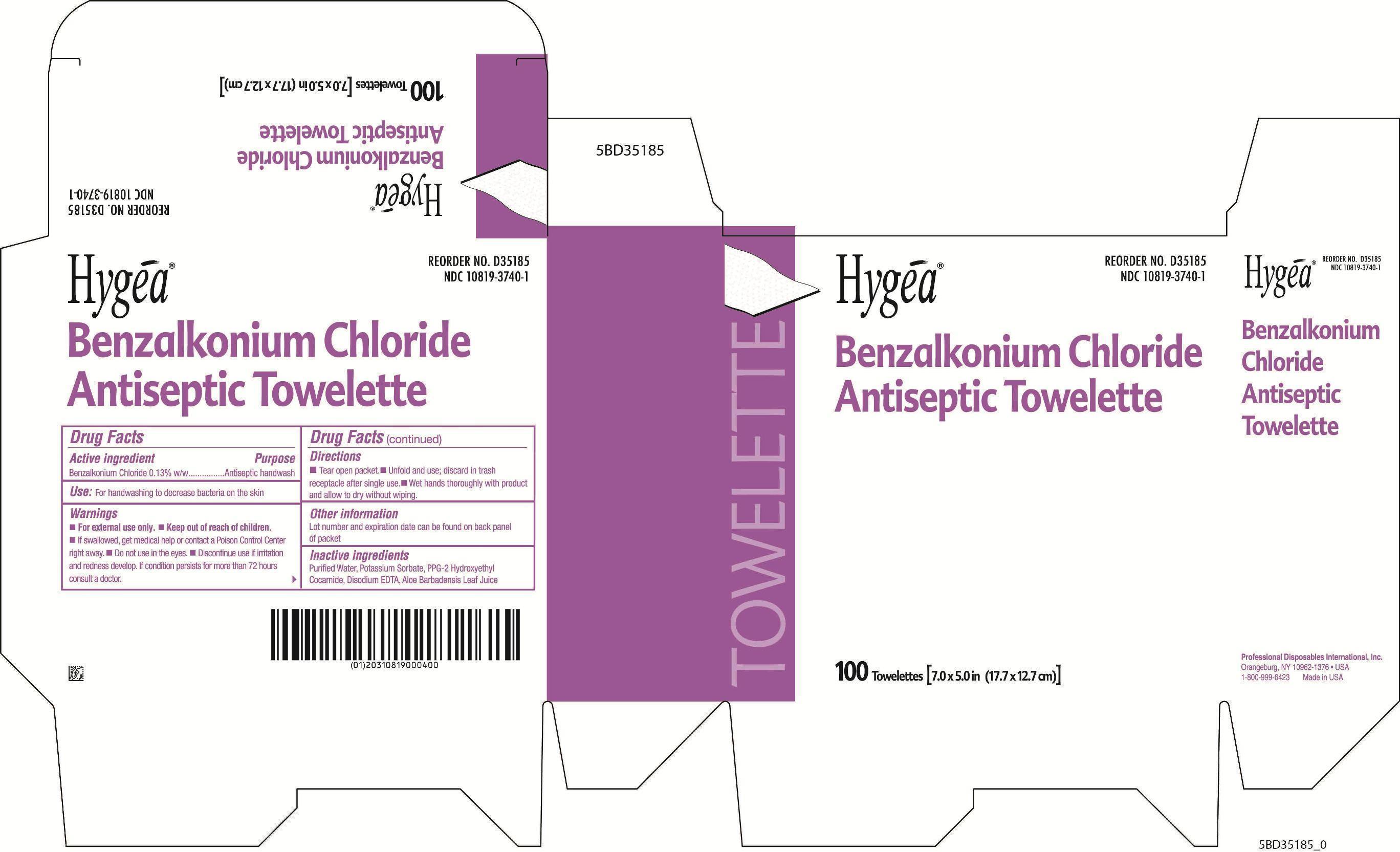 DRUG LABEL: Rx-Specimen Collection Kit
NDC: 69677-030 | Form: KIT | Route: ORAL
Manufacturer: MAS Management Group Inc.
Category: prescription | Type: HUMAN PRESCRIPTION DRUG LABEL
Date: 20180222

ACTIVE INGREDIENTS: FUROSEMIDE 20 mg/1 1; BENZALKONIUM CHLORIDE 0.0013 g/1 mL
INACTIVE INGREDIENTS: MODIFIED CORN STARCH (1-OCTENYL SUCCINIC ANHYDRIDE); LACTOSE MONOHYDRATE; MAGNESIUM STEARATE; STARCH, PREGELATINIZED CORN; SODIUM STARCH GLYCOLATE TYPE A CORN; WATER; POTASSIUM SORBATE; PPG-2 HYDROXYETHYL COCAMIDE; EDETATE DISODIUM; ALOE VERA LEAF

Rx-Specimen Collection Kit

WARNINGS AND PRECAUTIONS

Rx Only

COMPONENTS

Kit Contains

1 x Furosemide 20mg Tablet

3 x Benzalkonium Chloride Towelettes

1 x Sterile Urine Collection Cup with Temperature Strip

1 x Specimen Bag

Keep out of reach of children.